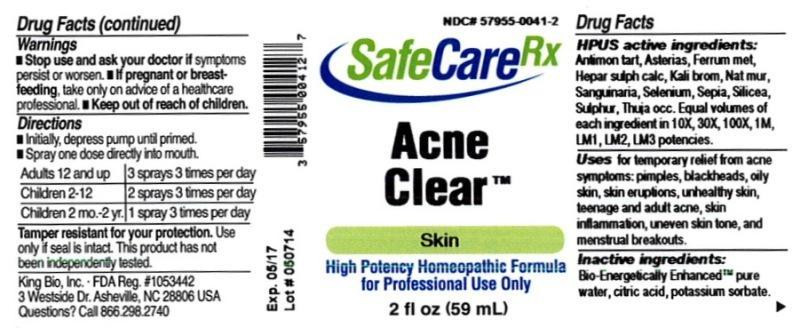 DRUG LABEL: Acne Clear
NDC: 57955-0041 | Form: LIQUID
Manufacturer: King Bio Inc.
Category: homeopathic | Type: HUMAN OTC DRUG LABEL
Date: 20140521

ACTIVE INGREDIENTS: ANTIMONY POTASSIUM TARTRATE 10 [hp_X]/59 mL; ASTERIAS RUBENS 10 [hp_X]/59 mL; IRON 10 [hp_X]/59 mL; CALCIUM SULFIDE 10 [hp_X]/59 mL; POTASSIUM BROMIDE 10 [hp_X]/59 mL; SODIUM CHLORIDE 10 [hp_X]/59 mL; SANGUINARIA CANADENSIS ROOT 10 [hp_X]/59 mL; SELENIUM 10 [hp_X]/59 mL; SEPIA OFFICINALIS JUICE 10 [hp_X]/59 mL; SILICON DIOXIDE 10 [hp_X]/59 mL; SULFUR 10 [hp_X]/59 mL; THUJA OCCIDENTALIS LEAFY TWIG 10 [hp_X]/59 mL
INACTIVE INGREDIENTS: WATER; CITRIC ACID MONOHYDRATE; POTASSIUM SORBATE

Acne Clear™

ACTIVE INGREDIENT

Drug Facts__________________________________________________________________________________________________________

HPUS active ingredients: Antimonium tartaricum, Asterias rubens, Ferrum metallicum, Hepar sulphuris calcareum, Kali bromatum, Natrum muriaticum, Sanguinaria canadensis, Selenium metallicum, Sepia, Silica, Sulphur, Thuja occidentalis. Equal volumes of each ingredient in 10X, 30X, 100X, 1M, LM1, LM2, LM3 potencies.

INDICATIONS AND USAGE

Uses for temporary relief from acne symptoms: pimples, blackheads, oily skin, skin eruptions, unhealthy skin, teenage and adult acne, skin inflammation, uneven skin tone, and menstrual breakouts.

Inactive Ingredients:

Bio-Energetically Enhanced™ pure water, citric acid and potassium sorbate.

Warnings

- Stop use and ask your doctor if symptoms persist or worsen.
- If pregnant or breast-feeding, take only on advice of a healthcare professional.

- Keep out of reach of children.

Directions

- Initially, depress pump until primed.
- Spray one dose directly into mouth.
- Adults 12 and up: 3 sprays 3 times per day.
- Children 2-12: 2 sprays 3 times per day.
- Children 2 mo-2 yr: 1 spray 3 times per day.

OTHER SAFETY INFORMATION

Tamper resistant for your protection. Use only if seal is intact. This product has not been independently tested.

PURPOSE

Uses for temporary relief from acne symptoms:

- pimples
- blackheads
- oily skin
- skin eruptions
- unhealthy skin
- teenage and adult acne
- skin inflammation
- uneven skin tone
- menstrual breakouts